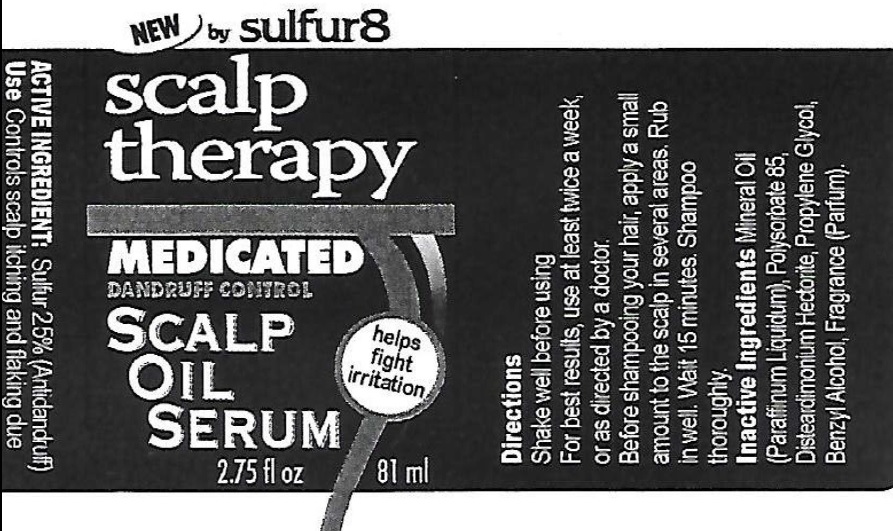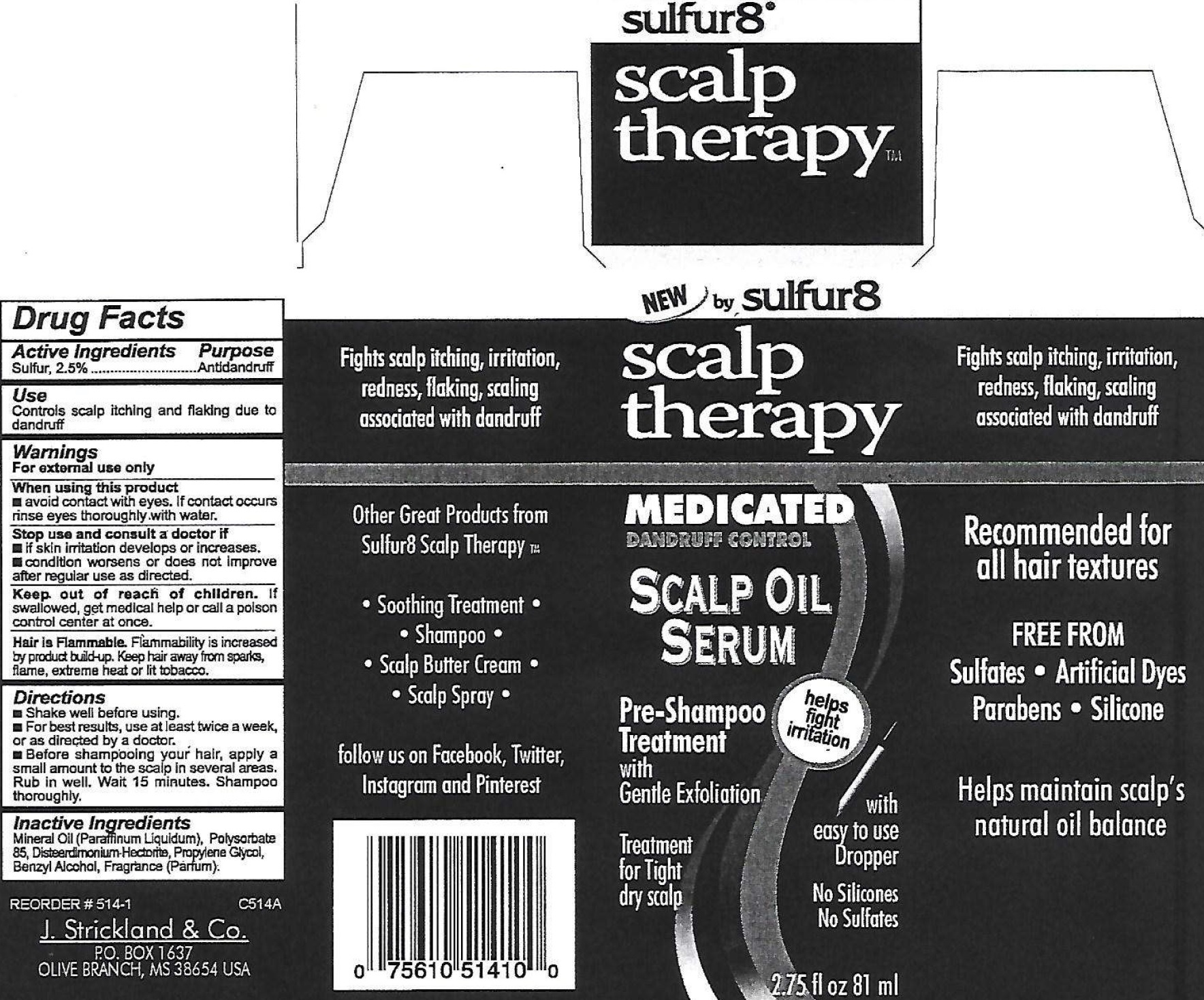 DRUG LABEL: Sulfur 8 Scalp Therapy Medicated Dandruff Control Scalp Oil Serum
NDC: 12022-034 | Form: SUSPENSION
Manufacturer: J. Strickland and Co.
Category: otc | Type: HUMAN OTC DRUG LABEL
Date: 20231021

ACTIVE INGREDIENTS: SULFUR 25 mg/1 mL
INACTIVE INGREDIENTS: MINERAL OIL; POLYSORBATE 85; DISTEARDIMONIUM HECTORITE; PROPYLENE GLYCOL; BENZYL ALCOHOL

Sulfur 8 Scalp Therapy Medicated Dandruff Control Scalp Oil Serum

Active Ingredient

Sulfur, 2.5%

Purpose

Antidandruff

Use

Controls scalp itching an flaking due to dandruff

Warnings

For external use only

When using this product

avoid contact with eyes. If contact occurs rinse eyes thoroughly with water.

Stop use and consult a doctor if

- if skin irritation develops or increases.
- condition worsens or does not improve after regular use as directed.

Keep out of reach of children.

If swallowed, get medical help or call a Poison Control Center at once.

Flammability is increased by proudct build-up. Keep hair away from sparks, flame, extreme heat or lit tobacco. Hair is Flammable.

Directions

- Shake well before using.
- For best results, use at least twice a week, or as directed by a doctor.
- Before shampooing your hair, apply a small amount to the scalp in several areas. Rub in well. Wait 15 minutes. Shampoo thoroughly.

Inactive Ingredients

Mineral Oil (Paraffinum Liquidum), Polysorbate 85, Disteardimonium Hectorite, Propylene Glycol, Benzyl Alcohol, Fragrance (Parfum)